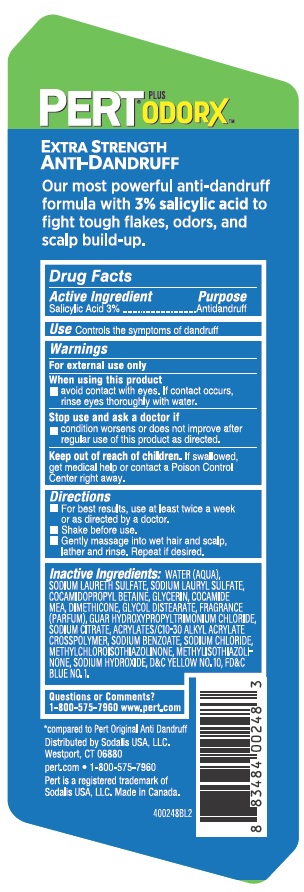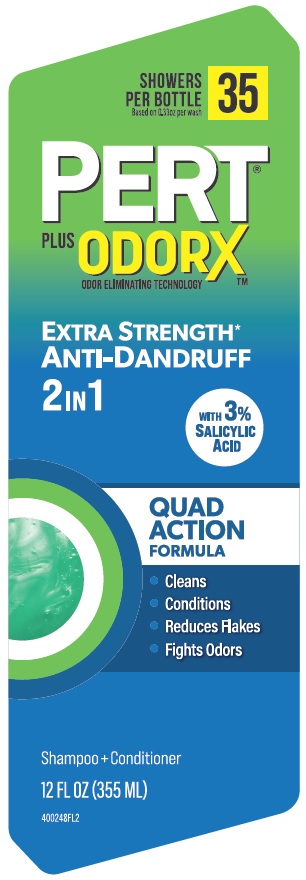 DRUG LABEL: Pert 2 in 1
NDC: 81277-803 | Form: SHAMPOO
Manufacturer: Sodalis USA, LLC
Category: otc | Type: HUMAN OTC DRUG LABEL
Date: 20250730

ACTIVE INGREDIENTS: SALICYLIC ACID 3 g/100 mL
INACTIVE INGREDIENTS: GUAR HYDROXYPROPYLTRIMONIUM CHLORIDE (1.7 SUBSTITUENTS PER SACCHARIDE); ACRYLATES/C10-30 ALKYL ACRYLATE CROSSPOLYMER (60000 MPA.S); GLYCERIN; COCO MONOETHANOLAMIDE; GLYCOL DISTEARATE; SODIUM CITRATE; WATER; DIMETHICONE; SODIUM BENZOATE; SODIUM CHLORIDE; D&C YELLOW NO. 10; COCAMIDOPROPYL BETAINE; FD&C BLUE NO. 1; SODIUM LAURETH SULFATE; METHYLISOTHIAZOLINONE; SODIUM LAURYL SULFATE; METHYLCHLOROISOTHIAZOLINONE; SODIUM HYDROXIDE

Pert 2 in 1 (SA) Extra Strength

Active ingredient

Salicylic Acid 3%

Purpose

Antidandruff

INDICATIONS AND USAGE

Use Controls the symptoms of dandruff

Warnings

For external use only

When using this product

- avoid contact with eyes. If contact occurs, rinse eyes thoroughly with water.

Stop use and ask a doctor if

- condition worsens or does not improve after regular use of this product as directed.

Keep out of reach of children. If swallowed, get medical help or contact a Poison Control Center right away.

Directions

- For best results, use at least twice a week or as directed by a doctor.
- Shake before use.
- Gently massage into wet hair and scalp, lather and rinse. Repeat if desired.

INACTIVE INGREDIENT

Inactive ingredients: Water (aqua), sodium laureth sulfate, sodium lauryl sulfate, cocamidopropyl betaine, glycerin, cocamide MEA, dimethicone, glycol distearate, fragrance (parfum), guar hydroxypropyltrimonium chloride, sodium citrate, acrylates/C10-30 alkyl acrylate crosspolymer, sodium benzoate, sodium chloride, methylchloroisothiazolinone, methylisothiazolinone, sodium hydroxide, D&C Yellow no. 10, FD&C Blue no. 1

Questions or Comments?

1-800-575-7960 www.pert.com

Distributed by: Sodalis USA, LLC.

Westport, CT 06880

pert.com • 1-800-575-7960

Pert is a registeed trademark of Sodalis USA, LLC.

Made in Canada.

400248BL2

PACKAGE LABEL

PERT®

EXTRA STRENGTH*

ANTI-DANDRUFF

2 IN 1

With 3% Salicylic Acid
QUAD ACTION FORMULA

- Cleans
- Conditions
- Reduces Flakes
- Fights Odors

SHAMPOO+CONDITIONER

12 FL OZ (355 mL)